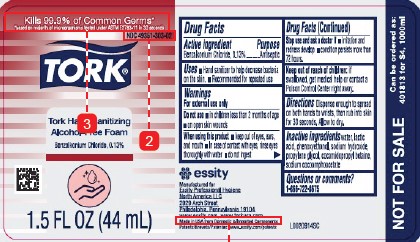 DRUG LABEL: Tork Hand Sanitizing Alcohol-Free Foam
NDC: 49351-303 | Form: LIQUID
Manufacturer: Essity Professional Hygiene North America LLC
Category: otc | Type: HUMAN OTC DRUG LABEL
Date: 20260204

ACTIVE INGREDIENTS: BENZALKONIUM CHLORIDE 1.3 mg/1 mL
INACTIVE INGREDIENTS: LACTIC ACID; PHENOXYETHANOL; SODIUM HYDROXIDE; PROPYLENE GLYCOL; COCAMIDOPROPYL BETAINE; SODIUM COCOAMPHOACETATE; WATER

Tork_Essity D19.001/D19AC
Essity Alcohol-Free Foam Hand Sanitizer

Active ingredient

Benzalkonium Chloride, 0.13%

Purpose

Antiseptic

Uses

- Hand Sanitizer to help decrease bacteria on the skin.
- Recommended for repeated use

Warnings

For external use only

Do not use

- in children less than 2 months of age
- on open skin wounds

When using this product

- keep out of eyes, ears, and mouth
- In case of contact with eyes, rinse eyes thoroughly with water
- do not ingest

Stop use and ask a doctor if

- irritation and redness develop
- condition persists more than 72 hours

Keep out of reach of children:

if swallowed, get medial help or contact a Posion Control Center right away.

Directions

Dispense enough to spread on both hands to wrists, then rub into skin for 30 seconds. Allow to dry.

Inactive ingredients

water, lactic acid, phenoxyethanol, sodium hydroxide, propylene glycol, cocamidopropyl betaine, sodium cocoamphoacetate

Questions or comments?

1-866-722-8675

ADVERSE REACTION

essity

Manufactured for

Essity Professional Hygiene

North America LLC

2929 Arch Street

Philadelphia, Pennsylvania 19104

www.essity.com, www.torkusa.com

Made in USA from Domestic & Imported Components

Patents/Brevets/Patentes: www.essisty.com/patents

NOT FOR SALE

Can be ordered as: 401813 for S4, 1000ml

Principal panel display

Kills 99.9% of Common Germs*

*based on majority of microorgnisms tested under ASTM E2783-11 in 30 seconds

NDC 49351-303-02

TORK®

Tork Hand Sanitizing

Alcohol-Free Foam

Benzalkonium Chloride, 0.13%

1.5 FL OZ (44 mL)